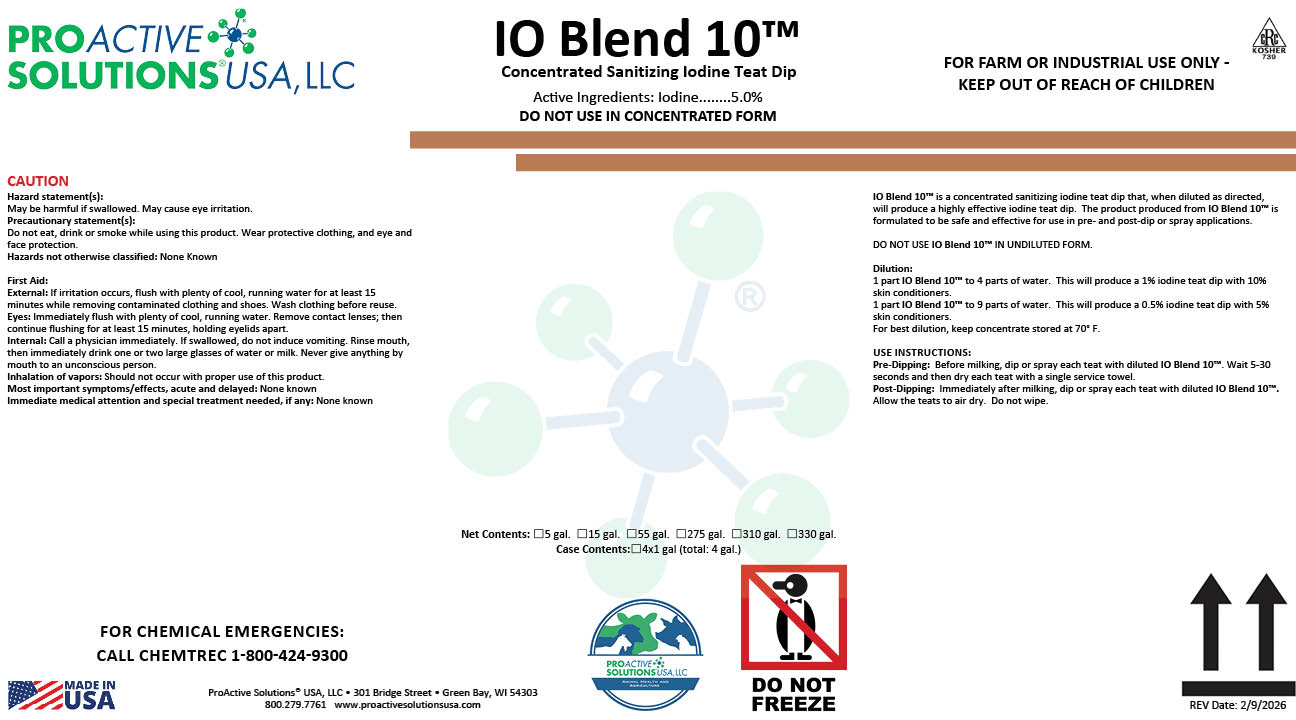 DRUG LABEL: IO Blend 10
NDC: 63927-4209 | Form: SOLUTION
Manufacturer: ProActive Solutions USA, LLC
Category: animal | Type: OTC ANIMAL DRUG LABEL
Date: 20260210

ACTIVE INGREDIENTS: IODINE 5 kg/100 kg

IO Blend 10

IO Blend 10™ is a concentrated sanitizing iodine teat dip that, when diluted as directed,
will produce a highly effective iodine teat dip. The product produced from IO Blend 10™ is
formulated to be safe and effective for use in pre- and post-dip or spray applications.
DO NOT USE IO Blend 10™ IN UNDILUTED FORM.
Dilution:
1 part IO Blend 10™ to 4 parts of water. This will produce a 1% iodine teat dip with 10%
skin conditioners.
1 part IO Blend 10™ to 9 parts of water. This will produce a 0.5% iodine teat dip with 5%
skin conditioners.
For best dilution, keep concentrate stored at 70° F.
USE INSTRUCTIONS:
Pre-Dipping: Before milking, dip or spray each teat with diluted IO Blend 10™. Wait 5-30
seconds and then dry each teat with a single service towel.
Post-Dipping: Immediately after milking, dip or spray each teat with diluted IO Blend 10™.
Allow the teats to air dry. Do not wipe.

Hazard statement(s):
May be harmful if swallowed. May cause eye irritation.
Precautionary statement(s):
Do not eat, drink or smoke while using this product. Wear protective clothing, and eye and
face protection.
Hazards not otherwise classified: None Known
First Aid:
External: If irritation occurs, flush with plenty of cool, running water for at least 15
minutes while removing contaminated clothing and shoes. Wash clothing before reuse.
Eyes: Immediately flush with plenty of cool, running water. Remove contact lenses; then
continue flushing for at least 15 minutes, holding eyelids apart.
Internal: Call a physician immediately. If swallowed, do not induce vomiting. Rinse mouth,
then immediately drink one or two large glasses of water or milk. Never give anything by
mouth to an unconscious person.
Inhalation of vapors: Should not occur with proper use of this product.
Most important symptoms/effects, acute and delayed: None known
Immediate medical attention and special treatment needed, if any: None known